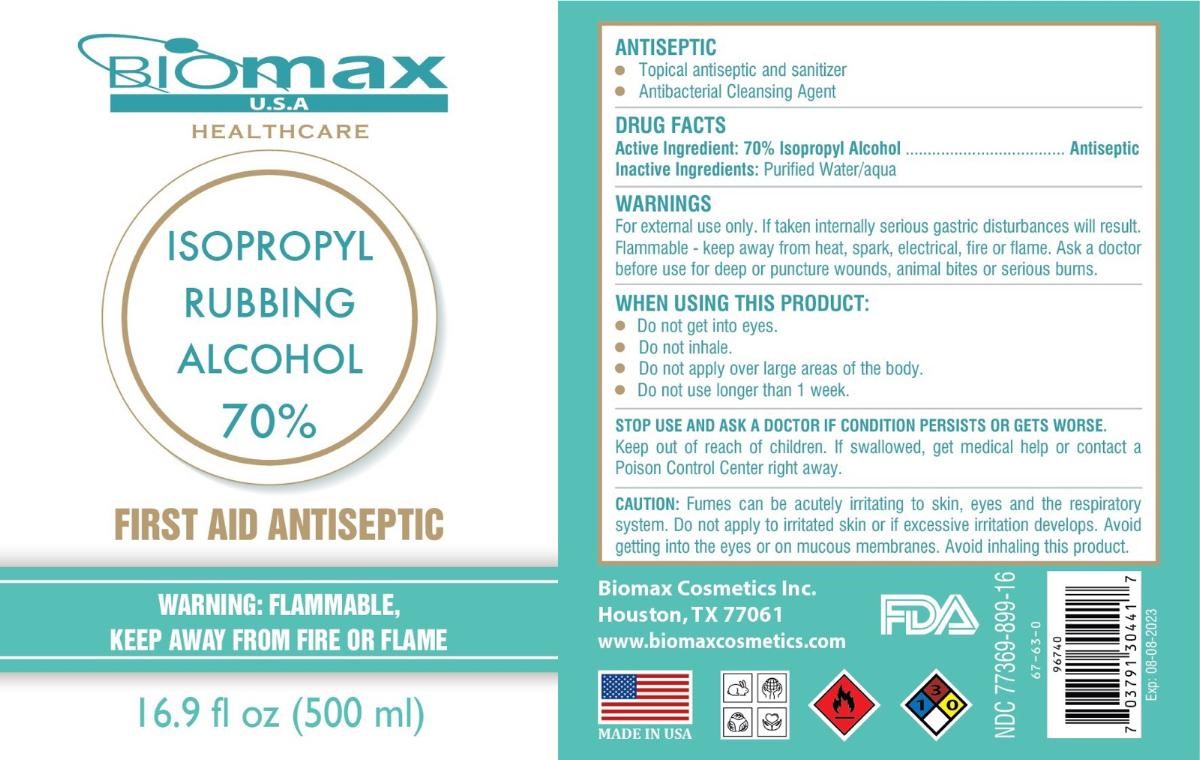 DRUG LABEL: Biomax USA
NDC: 77369-899 | Form: LIQUID
Manufacturer: Biomax Cosmetics
Category: otc | Type: HUMAN OTC DRUG LABEL
Date: 20200810

ACTIVE INGREDIENTS: ISOPROPYL ALCOHOL 70 mL/100 mL
INACTIVE INGREDIENTS: WATER

Biomax FIRST AID ANTISEPTIC

Active Ingredient: 70% Isopropyl Alcohol

Purpose: Antiseptic

USES

• hand sanitizer to decrease bacteria on the skin

• recommended for repeated use

• for use when soap and water are not available

Inactive Ingredients: Purified Water/aqua

WARNINGS

For external use only. If taken internally serious gastric disturbances will result.

Flammable - keep away from heat, spark, electrical, fire or flame. Ask a doctor before use for deep or puncture wounds, animal bites or serious burns.

WHEN USING THIS PRODUCT:

• Do not get into eyes.

• Do not inhale.

• Do not apply over large areas of the body.

• Do not use longer than 1 week.

STOP USE AND ASK A DOCTOR IF CONDITION PERSISTS OR GETS WORSE.

Keep out of reach of children. If swallowed, get medical help or contact a Poison Control Center right away.

DIRECTIONS

• supervise children under 6 years of age when using this product to avoid swallowing

HEALTHCARE

ISOPROPYL RUBBING ALCOHOL 70%

WARNING: FLAMMABLE,

KEEP AWAY FROM FIRE OR FLAME

ANTISEPTIC

• Topical antiseptic and sanitizer

• Antibacterial Cleansing Agent

CAUTION: Fumes can be acutely irritating to skin, eyes and the respiratory system. Do not apply to irritated skin or if excessive irritation develops. Avoid getting into the eyes or on mucous membranes. Avoid inhaling this product.

Biomax Cosmetics Inc.

Houston, TX 77061

www.biomaxcosmetics.com

MADE IN USA